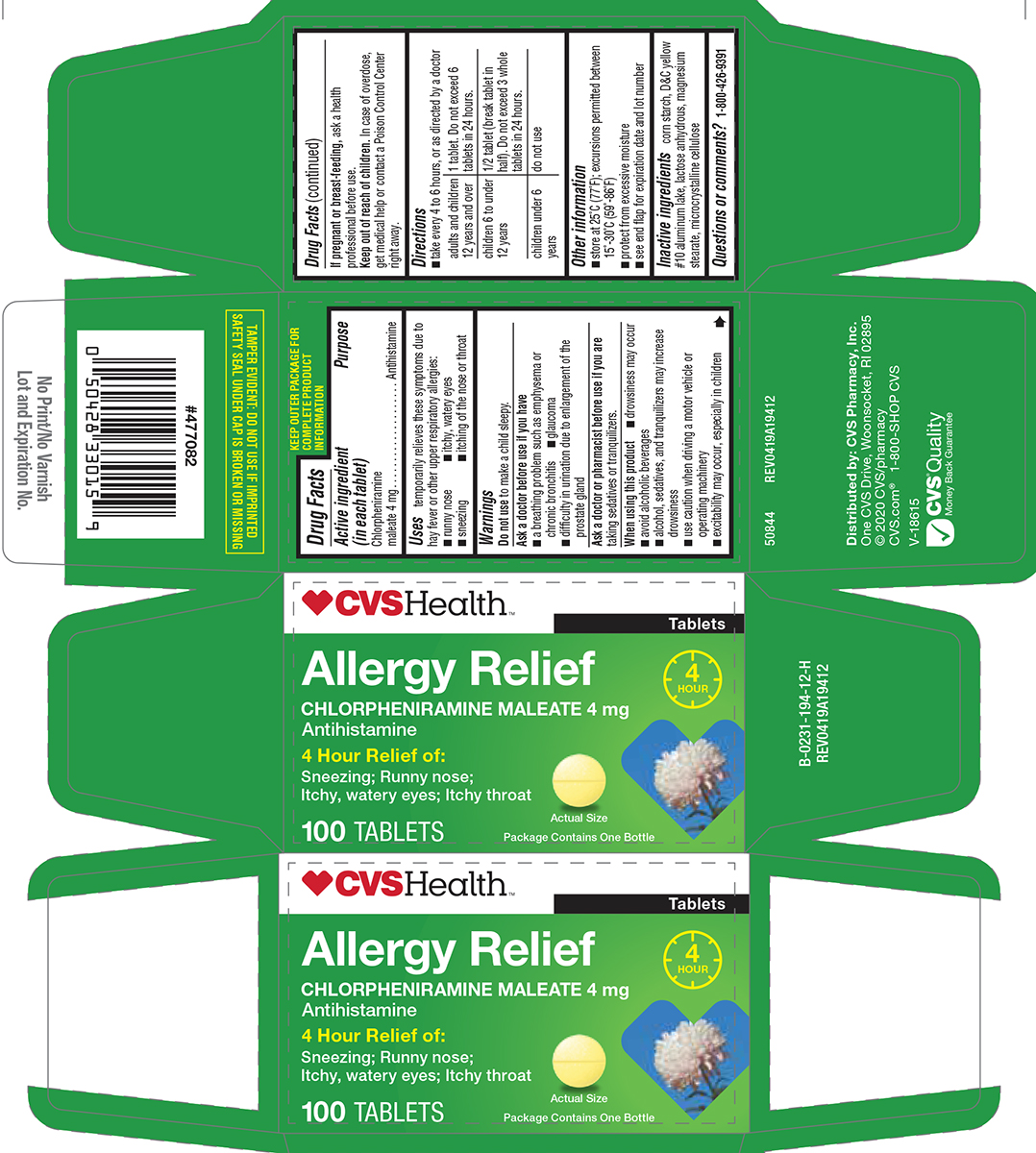 DRUG LABEL: Allergy Relief
NDC: 69842-194 | Form: TABLET
Manufacturer: CVS PHARMACY
Category: otc | Type: HUMAN OTC DRUG LABEL
Date: 20250903

ACTIVE INGREDIENTS: CHLORPHENIRAMINE MALEATE 4 mg/1 1
INACTIVE INGREDIENTS: STARCH, CORN; D&C YELLOW NO. 10 ALUMINUM LAKE; ANHYDROUS LACTOSE; MAGNESIUM STEARATE; MICROCRYSTALLINE CELLULOSE

CVS 44-194

Active ingredient (in each tablet)

Chlorpheniramine maleate 4 mg

Purpose

Antihistamine

Uses

temporarily relieves these symptoms due to hay fever or other upper respiratory allergies:

- runny nose
- sneezing
- itchy, watery eyes
- itching of the nose or throat

Warnings

Do not use

to make a child sleepy.

Ask a doctor before use if you have

- a breathing problem such as emphysema or chronic bronchitis
- glaucoma
- difficulty in urination due to enlargement of the prostate gland

Ask a doctor or pharmacist before use if you are

taking sedatives or tranquilizers.

When using this product

- drowsiness may occur
- avoid alcoholic beverages
- alcohol, sedatives, and tranquilizers may increase drowsiness
- use caution when driving a motor vehicle or operating machinery
- excitability may occur, especially in children

If pregnant or breast-feeding,

ask a health professional before use.

Keep out of reach of children.

In case of overdose, get medical help or contact a Poison Control Center right away.

Directions

- take every 4 to 6 hours, or as directed by a doctor

adults and children 12 years and over | 1 tablet. Do not exceed 6 tablets in 24 hours.
children 6 to under 12 years | 1/2 tablet (break tablet in half). Do not exceed 3 whole tablets in 24 hours.
children under 6 years | do not use

Other information

- store at 25ºC (77ºF); excursions permitted between 15º-30ºC (59º-86ºF)
- protect from excessive moisture
- see end flap for expiration date and lot number

Inactive ingredients

corn starch, D&C yellow #10 aluminum lake, lactose anhydrous, magnesium stearate, microcrystalline cellulose

Questions or comments?

1-800-426-9391

Principal Display Panel

CVS Health™

Tablets

Allergy Relief

CHLORPHENIRAMINE MALEATE 4 mg
Antihistamine

4 Hour Relief of:

Sneezing; Runny nose;
Itchy, watery eyes; Itchy throat

Actual Size

Package Contains One Bottle

100 TABLETS

TAMPER EVIDENT: DO NOT USE IF IMPRINTED
SAFETY SEAL UNDER CAP IS BROKEN OR MISSING

50844 REV0419A19412

Distributed by: CVS Pharmacy, Inc.
One CVS Drive, Woonsocket, RI 02895
© 2020 CVS/pharmacy
CVS.com® 1-800-SHOP CVS

V-18615

CVS® Quality
Money Back Guarantee

CVS Health 44-194